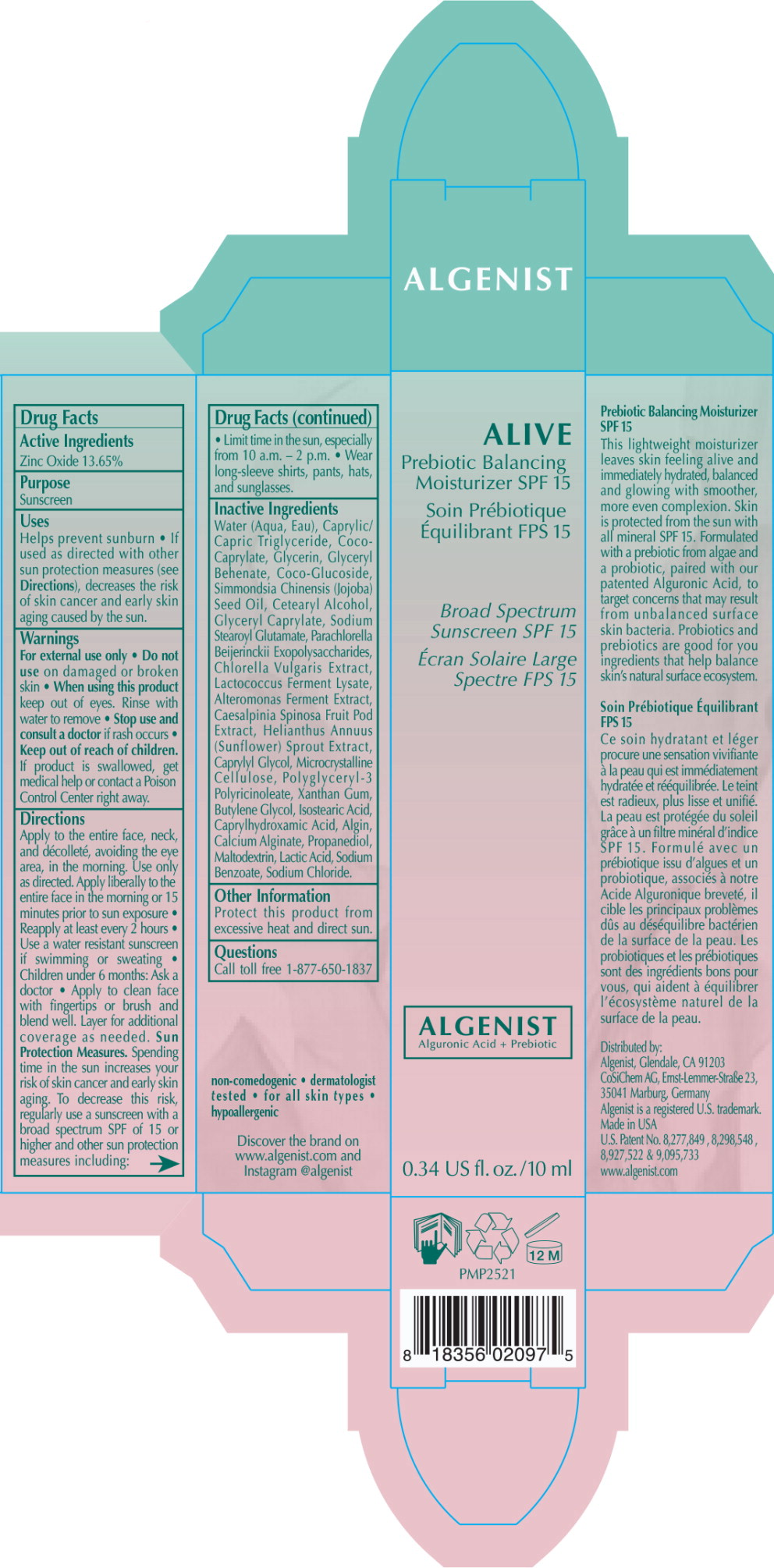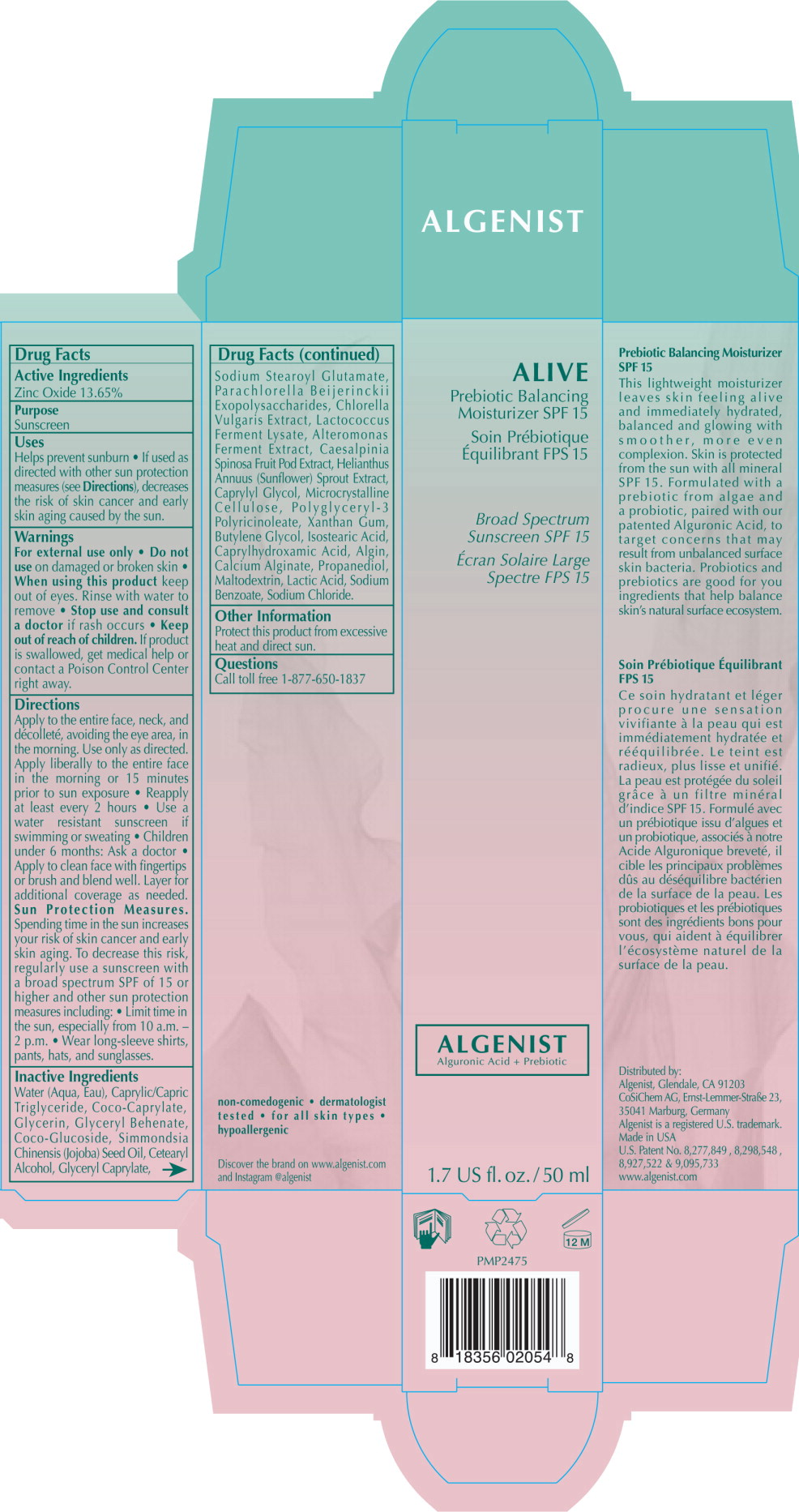 DRUG LABEL: Alive Prebiotic Balancing Moisturizer SPF 15
NDC: 71047-262 | Form: LOTION
Manufacturer: Algenist, LLC
Category: otc | Type: HUMAN OTC DRUG LABEL
Date: 20180914

ACTIVE INGREDIENTS: ZINC OXIDE 0.1365 mg/1 mL
INACTIVE INGREDIENTS: WATER; MEDIUM-CHAIN TRIGLYCERIDES; COCO-CAPRYLATE; GLYCERIN; GLYCERYL MONOBEHENATE; COCO GLUCOSIDE; JOJOBA OIL; CETOSTEARYL ALCOHOL; GLYCERYL MONOCAPRYLATE; SODIUM STEAROYL GLUTAMATE; CAPRYLYL GLYCOL; MICROCRYSTALLINE CELLULOSE; POLYGLYCERYL-3 RICINOLEATE; XANTHAN GUM; BUTYLENE GLYCOL; ISOSTEARIC ACID; CAPRYLHYDROXAMIC ACID; SODIUM ALGINATE; CALCIUM ALGINATE; PROPANEDIOL; MALTODEXTRIN; CHLORELLA VULGARIS; CAESALPINIA SPINOSA FRUIT POD; LACTIC ACID, UNSPECIFIED FORM; SODIUM BENZOATE; SODIUM CHLORIDE

Drug Facts

Active Ingredients

Zinc Oxide 13.65%

Purpose

Sunscreen

Uses

Helps prevent sunburn

- If used as directed with other sun protection measures (see Directions), decreases the risk of skin cancer and early skin aging caused by the sun.

Warnings

For external use only

- Do not use on damaged or broken skin

- When using this product keep out of eyes. Rinse with water to remove

- Stop use and consult a doctor if rash occurs

- Keep out of reach of children. If product is swallowed, get medical help or contact a Poison Control Center right away.

Directions

Apply to the entire face, neck, and décolleté, avoiding the eye area, in the morning. Use only as directed. Apply liberally to the entire face in the morning or 15 minutes prior to sun exposure

- Reapply at least every 2 hours
- Use a water resistant sunscreen if swimming or sweating
- Children under 6 months: Ask a doctor
- Apply to clean face with fingertips or brush and blend well. Layer for additional coverage as needed.

Sun Protection Measures. Spending time in the sun increases your risk of skin cancer and early skin aging. To decrease this risk, regularly use a sunscreen with a broad spectrum SPF of 15 or higher and other sun protection measures including:

- Limit time in the sun, especially from 10 a.m. – 2 p.m.
- Wear long-sleeve shirts, pants, hats, and sunglasses.

Inactive Ingredients

Water (Aqua, Eau), Caprylic/ Capric Triglyceride, Coco-Caprylate, Glycerin, Glyceryl Behenate, Coco-Glucoside, Simmondsia Chinensis (Jojoba) Seed Oil, Cetearyl Alcohol, Glyceryl Caprylate, Sodium Stearoyl Glutamate, Parachlorella Beijerinckii Exopolysaccharides, Chlorella Vulgaris Extract, Lactococcus Ferment Lysate, Alteromonas Ferment Extract, Caesalpinia Spinosa Fruit Pod Extract, Helianthus Annuus (Sunflower) Sprout Extract, Caprylyl Glycol, Microcrystalline Cellulose, Polyglyceryl-3 Polyricinoleate, Xanthan Gum, Butylene Glycol, Isostearic Acid, Caprylhydroxamic Acid, Algin, Calcium Alginate, Propanediol, Maltodextrin, Lactic Acid, Sodium Benzoate, Sodium Chloride.

Other Information

Protect this product from excessive heat and direct sun.

Questions

Call toll free 1-877-650-1837

Principal Display Panel - 10 mL Box Label

ALIVE

Prebiotic Balancing
Moisturizer SPF 15

Soin Prébiotique
Équilibrant FPS 15

Broad Spectrum
Sunscreen SPF 15

Écran Solaire Large
Spectre FPS 15

ALGENIST
Alguronic Acid + Prebiotic

0.34 US fl. oz. / 10 ml

Principal Display Panel - 50 mL Box Label

ALIVE

Prebiotic Balancing
Moisturizer SPF 15

Soin Prébiotique
Équilibrant FPS 15

Broad Spectrum
Sunscreen SPF 15

Écran Solaire Large
Spectre FPS 15

ALGENIST
Alguronic Acid + Prebiotic

1.7 US fl. oz. / 50 ml